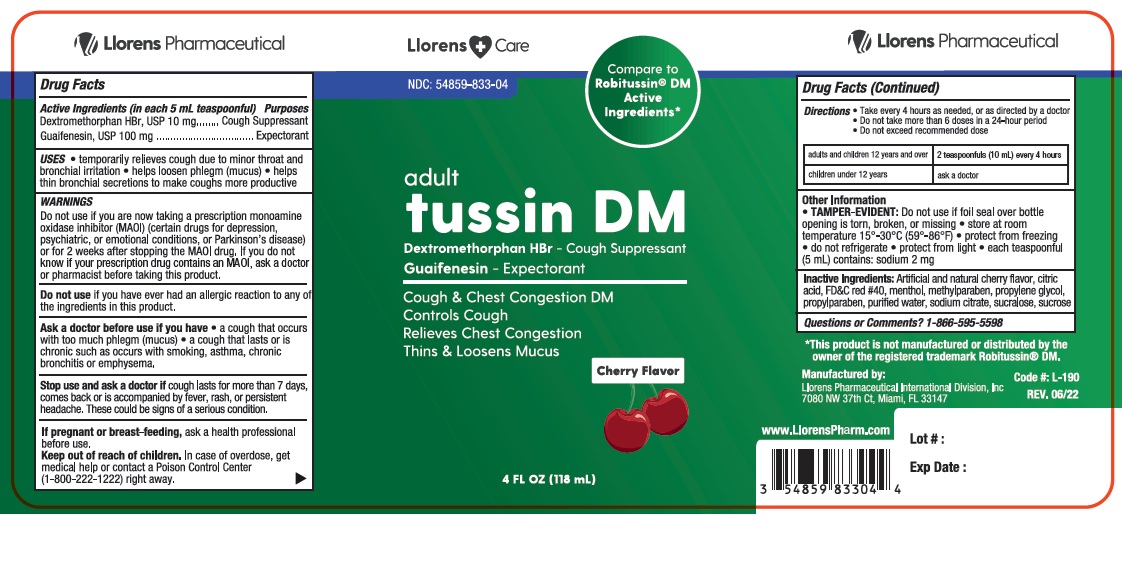 DRUG LABEL: Llorens Care Tussin DM
NDC: 54859-833 | Form: LIQUID
Manufacturer: Llorens Pharmaceutical International Division, Inc.
Category: otc | Type: HUMAN OTC DRUG LABEL
Date: 20251231

ACTIVE INGREDIENTS: DEXTROMETHORPHAN HYDROBROMIDE 10 mg/5 mL; GUAIFENESIN 100 mg/5 mL
INACTIVE INGREDIENTS: ANHYDROUS CITRIC ACID; FD&C RED NO. 40; MENTHOL; METHYLPARABEN; PROPYLENE GLYCOL; PROPYLPARABEN; WATER; SODIUM CITRATE; SUCRALOSE; SUCROSE

LC Tussin DM 833

ACTIVE INGREDIENT

In each 5 mL

Dextromethorphan - 10 mg

Guaifenesin - 100 mg

Purpose

Cough Suppressant

Expectorant

Uses

- temporarily relieves cough due to minor throat and bronchial irritation
- helps loosen phlegm (mucus)
- helps thin bronchial secretions to make coughs more productive

Warnings

Do not use if you are now taking a prescritpion monamine oxidase inhibitor (MAOI) (certain drugs for depression, psychiatric, or emotional conditions, or Parkinson's diesease), or for 2 weeks after stopping the MAOI drug. If you do not know if your prescirption drug contains an MAOI, aska doctor or pharmacist before taking this product.

Do not useif you have ever had an allergic reaction to any of the ingredients in this product.

Ask a doctor before use if you have

- cough that occurs with too much phlegm (mucus)
- cough that lasts or is chronic such as occurs with smoking, asthma, chronic bronchitis, or emphysema

Stop use and ask a doctor if cough lasts for more than 7 days, comes back, or is accompanied by fever, rash, or head that lasts. These could be signs of a serious condition.

PREGNANCY OR BREAST FEEDING

If pregnant or breast-feeing, ask a health professional before use.

Keep out of reach of children. In case of overdose, get medical help or contact a Poison Control Center (1-800-222-1222)right away.

Directions:

- take every 4 hours as needed, or as directed by a doctor
- do not take more than 6 doses in 24 hours
- do not exceed recommended dose

Age | Dose
Adults and children over 12 years and over | 2 teaspoonfuls (10 mL) every 4 hours
Children under 12 years | ask a doctor

INACTIVE INGREDIENT

Inactive ingredients artificial and natural cherry flavor, citric acid, FD&C #40, menthol, methylparaben, propylene glycol, propylparaben, purified water, sodium citrate, sucralose, sucrose.

Questions or comments? 1-866-595-5598

RECENT MAJOR CHANGES

fix typos